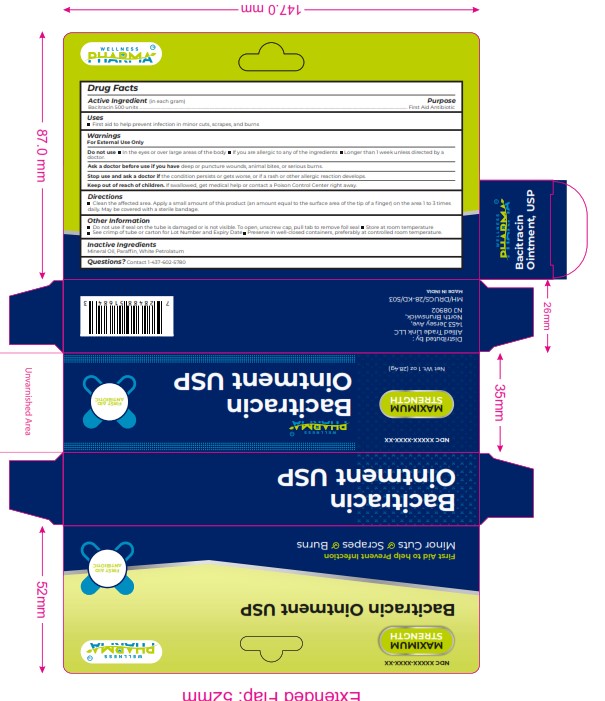 DRUG LABEL: BACITRACIN
NDC: 84387-002 | Form: OINTMENT
Manufacturer: ALLIED TRADE LINK LLC
Category: otc | Type: HUMAN OTC DRUG LABEL
Date: 20241112

ACTIVE INGREDIENTS: BACITRACIN 500 [USP'U]/1 g
INACTIVE INGREDIENTS: WHITE PETROLATUM; MINERAL OIL; PARAFFIN

BACITRACIN

ACTIVE INGRIDIENT

Active Ingredient (in each gram) Purpose

Bacitracin 500 units ............................................................................................................................................................................................................................................................. First Aid Antibiotic

USES

First aid to help prevent infection in minor cuts, scrapes, and burns

WARNINGS

For External Use Only

Do not use In the eyes or over large areas of the body If you are allergic to any of the ingredients Longer than 1 week unless directed by a
doctor.

Ask a doctor before use if you have deep or puncture wounds, animal bites, or serious burns.

DO NOT USE

Stop use and ask a doctor if the condition persists or gets worse, or if a rash or other allergic reaction develops.

Keep out of reach of children. If swallowed, get medical help or contact a Poison Control Center right away.

DIRECTION

Clean the affected area. Apply a small amount of this product (an amount equal to the surface area of the tip of a ﬁnger) on the area 1 to 3 times
daily. May be covered with a sterile bandage.

OTHER INFORMATION

Do not use if seal on the tube is damaged or is not visible. To open, unscrew cap, pull tab to remove foil seal Store at room temperature
See crimp of tube or carton for Lot Number and Expiry Date Preserve in well-closed containers, preferably at controlled room temperature.

INACTIVE INGREDIENTS

Mineral Oil, Parafﬁn, White Petrolatum

dosage and administration

Clean the affected area and dry thoroughly Apply a thin layer of the cream over affected area twice daily (morning and night) or as directed by
a doctor Supervise children in the use of this product For athlete's foot: Pay special attention to spaces between the toes; wear well-ﬁtting,
ventilated shoes, and change shoes and socks at least once daily For athlete's foot and ringworm, use daily for 4 weeks For jock itch, use daily for
2 weeks If condition persists longer, consult a doctor This product is not effective on the scalp or nails

Active Ingredient (in each gram) Purpose Bacitracin 500 units ............................................................................................................................................................................................................................................................. First Aid Antibiotic

Active Ingredient (in each gram) Purpose
Bacitracin 500 units ............................................................................................................................................................................................................................................................. First Aid Antibiotic